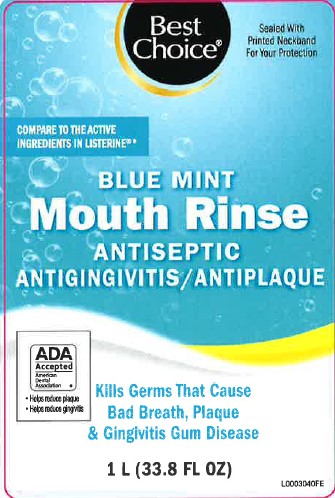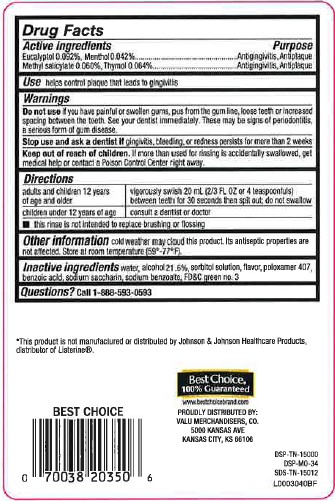 DRUG LABEL: Antispetic
NDC: 63941-664 | Form: MOUTHWASH
Manufacturer: Valu Merchandisers Company
Category: otc | Type: HUMAN OTC DRUG LABEL
Date: 20260216

ACTIVE INGREDIENTS: EUCALYPTOL 0.92 mg/1 mL; MENTHOL 0.42 mg/1 mL; METHYL SALICYLATE 0.6 mg/1 mL; THYMOL 0.64 mg/1 mL
INACTIVE INGREDIENTS: FD&C GREEN NO. 3; WATER; ALCOHOL; SORBITOL; POLOXAMER 407; BENZOIC ACID; SACCHARIN SODIUM; SODIUM BENZOATE

Best Choice 664.003/664AT rev 2 664AU
Blue Mint Antiseptic Mouthrinse

Active ingredients

Eucalyptol 0.092%

Menthol 0.042%

Methyl salicylate 0.060%

Thymol 0.064%

Purpose

Antigingivitis, antiplaque

Use

helps control plaque that leads to gingivitis

Warnings

for this product

Do not use

if you have painful or swollen gums, pus from the gum line, loose teeth or increased spacing between the teeth. See your dentist immediately. These may be signs of periodontitis, a serious form of gum disease.

Stop use and ask a dentist if

gingivitis, bleeding, or redness persists for more than 2 weeks.

Keep out of reach of children.

If more than used for rinsing is accidentally swallowed, get medical help or contact a Poison Control Center right away.

Directions

adults and children 12 years of age and older - vigorously swish 20 mL (2/3 FL OZ or 4 teaspoonfuls) between teeth for 30 seconds then spit out; do not swallow

children under 12 years of age - consult a dentist or doctor

- this rinse is not intended to replace brushing or flossing

Other information

cold weather may cloud this product. Its antiseptic properties are not affected. Store at room temperature (59°-77°F).

Inactive ingredients

water, alcohol 21.6%, sorbitol solution, poloxamer 407, benzoic acid, sodium saccharin, sodium benzoate, flavor, FD&C green no.3

Questions?

Call 1-888-593-0593

Disclaimer

*This product is not manufactured or distribted by Johnson & Johnson Healthcare Products, distributor of Listerine.

Adverse Reactions

Best Choice®

100% Guaranteed

www.bestchoicebrand.com

PROUDLY DISTRIBUTED BY:

VALU MERCHANDISERS, CO.

5000 KANSAS AVE

KANSAS CITY, MO 66106

DSP-TN-15000

DSP-MO-34

SDS-TN-15012

principal display panel

Best

Choice®

Sealed With Printed Neckband For Your Protection

COMPARE TO THE ACTIVE INGREDETS IN LISTERINE®*

BLUE MINT

MOUTH RINSE

ANTISEPTIC

ANTIGINGIVITIS / ANTIPLAQUE

ADA Accepted

American Dental Association

- Helps reduce plaque
- Helps reduce gingivitis

Kills Germs That Cause Bad Breath, Plaque & Gingivitis Gum Disease

1 L (33.8 FL OZ)